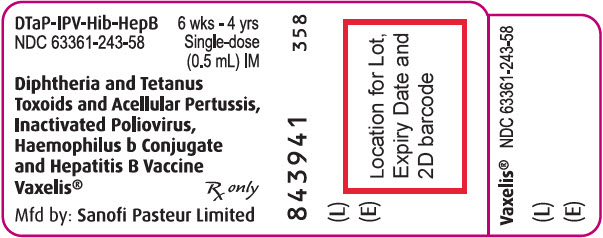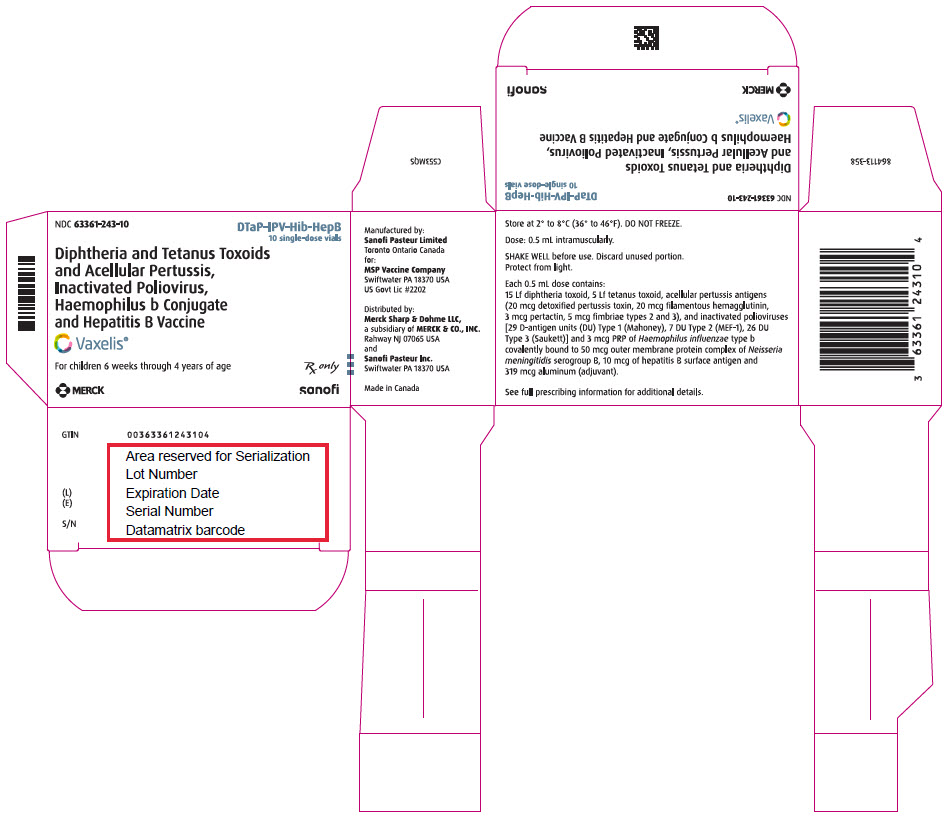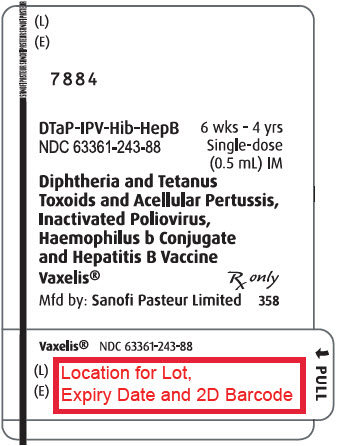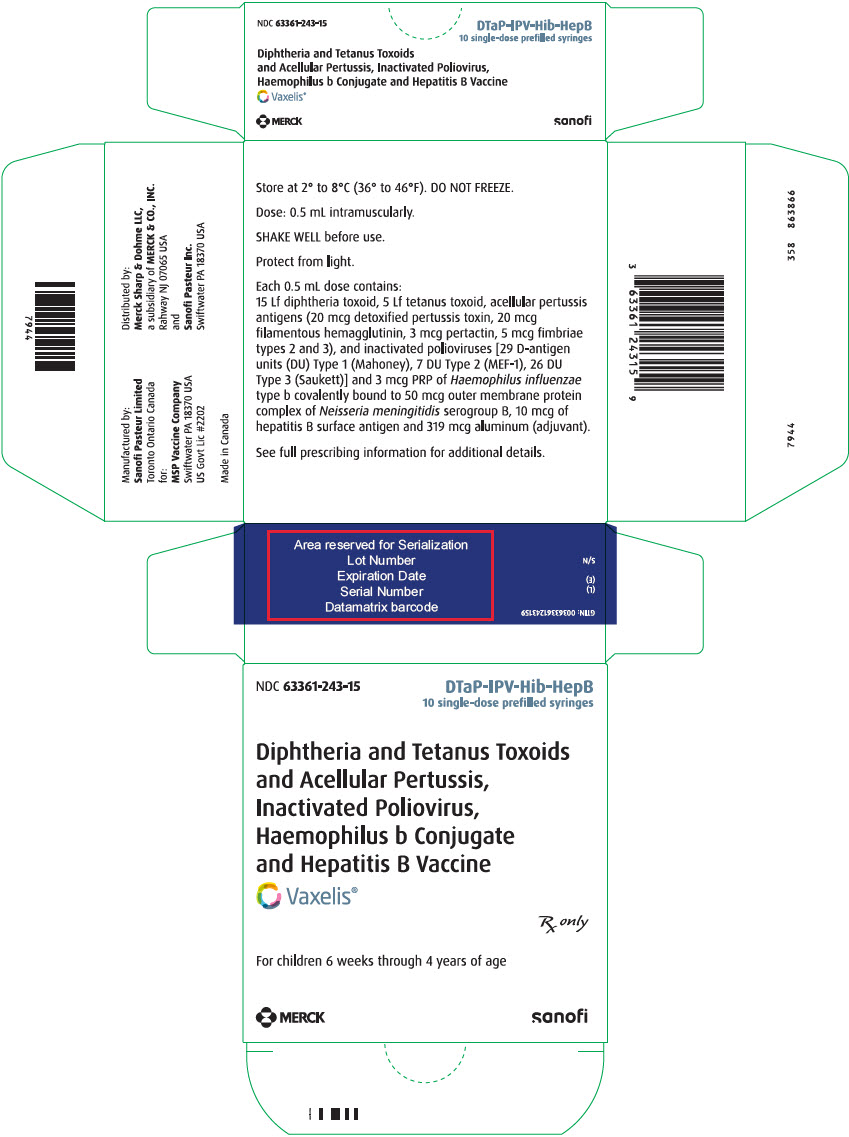 DRUG LABEL: VAXELIS
NDC: 63361-243 | Form: INJECTION, SUSPENSION
Manufacturer: MSP Vaccine Company
Category: other | Type: VACCINE LABEL
Date: 20251112

ACTIVE INGREDIENTS: CORYNEBACTERIUM DIPHTHERIAE TOXOID ANTIGEN (FORMALDEHYDE INACTIVATED) 15 [Lf]/0.5 mL; CLOSTRIDIUM TETANI TOXOID ANTIGEN (FORMALDEHYDE INACTIVATED) 5 [Lf]/0.5 mL; BORDETELLA PERTUSSIS TOXOID ANTIGEN (GLUTARALDEHYDE INACTIVATED) 20 ug/0.5 mL; BORDETELLA PERTUSSIS FILAMENTOUS HEMAGGLUTININ ANTIGEN (FORMALDEHYDE INACTIVATED) 20 ug/0.5 mL; BORDETELLA PERTUSSIS PERTACTIN ANTIGEN 3 ug/0.5 mL; BORDETELLA PERTUSSIS FIMBRIAE 2/3 ANTIGEN 5 ug/0.5 mL; POLIOVIRUS TYPE 1 ANTIGEN (FORMALDEHYDE INACTIVATED) 29 [D'ag'U]/0.5 mL; POLIOVIRUS TYPE 2 ANTIGEN (FORMALDEHYDE INACTIVATED) 7 [D'ag'U]/0.5 mL; POLIOVIRUS TYPE 3 ANTIGEN (FORMALDEHYDE INACTIVATED) 26 [D'ag'U]/0.5 mL; HEPATITIS B VIRUS SUBTYPE ADW HBSAG SURFACE PROTEIN ANTIGEN 10 ug/0.5 mL; HAEMOPHILUS INFLUENZAE TYPE B CAPSULAR POLYSACCHARIDE MENINGOCOCCAL OUTER MEMBRANE PROTEIN CONJUGATE ANTIGEN 3 ug/0.5 mL
INACTIVE INGREDIENTS: POLYSORBATE 80 28 ug/0.5 mL; FORMALDEHYDE 14 ug/0.5 mL; GLUTARAL 50 ng/0.5 mL; ALBUMIN BOVINE 50 ng/0.5 mL; NEOMYCIN 5 ng/0.5 mL; POLYMYXIN B SULFATE 25 ng/0.5 mL; STREPTOMYCIN 200 ng/0.5 mL; AMMONIUM THIOCYANATE 0.125  ug/0.5 mL; GI-6207 0.1 ug/0.5 mL; WATER

HIGHLIGHTS OF PRESCRIBING INFORMATION

These highlights do not include all the information needed to use VAXELIS safely and effectively. See full prescribing information for VAXELIS.
VAXELIS® (Diphtheria and Tetanus Toxoids and Acellular Pertussis, Inactivated Poliovirus, Haemophilus b Conjugate and Hepatitis B Vaccine)
Suspension for Intramuscular Injection
Initial U.S. Approval: 2018

1 INDICATIONS AND USAGE

VAXELIS is a vaccine indicated for active immunization to prevent diphtheria, tetanus, pertussis, poliomyelitis, hepatitis B, and invasive disease due to Haemophilus influenzae type b. VAXELIS is approved for use as a 3-dose series in children from 6 weeks through 4 years of age (prior to the 5th birthday). (1)

2 DOSAGE AND ADMINISTRATION

The 3-dose immunization series consists of a 0.5 mL intramuscular injection, administered at 2, 4, and 6 months of age. (2.1)

3 DOSAGE FORMS AND STRENGTHS

Suspension for injection (0.5 mL dose) available in single-dose vials and prefilled syringes. (3)

4 CONTRAINDICATIONS

- Severe allergic reaction (e.g., anaphylaxis) to a previous dose of VAXELIS, any ingredient of VAXELIS, or any other diphtheria toxoid, tetanus toxoid, pertussis-containing vaccine, inactivated poliovirus vaccine, hepatitis B vaccine, or Haemophilus influenzae type b vaccine. (4.1)
- Encephalopathy within 7 days of a previous pertussis-containing vaccine with no other identifiable cause. (4.2)
- Progressive neurologic disorder until a treatment regimen has been established and the condition has stabilized. (4.3)

5 WARNINGS AND PRECAUTIONS

- Carefully consider benefits and risks before administering VAXELIS to persons with a history of:
  - fever ≥40.5°C (≥105°F), hypotonic-hyporesponsive episode (HHE) or persistent, inconsolable crying lasting ≥3 hours within 48 hours after a previous pertussis-containing vaccine. (5.2)
  - seizures within 3 days after a previous pertussis-containing vaccine. (5.2)
- If Guillain-Barré syndrome occurred within 6 weeks of receipt of a prior vaccine containing tetanus toxoid, the risk for Guillain-Barré syndrome may be increased following VAXELIS. (5.3)
- Apnea following intramuscular vaccination has been observed in some infants born prematurely. The decision about when to administer an intramuscular vaccine, including VAXELIS, to an infant born prematurely should be based on consideration of the individual infant's medical status and the potential benefits and possible risks of vaccination. (5.5)
- Urine antigen detection may not have definitive diagnostic value in suspected H. influenzae type b disease following vaccination with VAXELIS. (5.7) (7.1)

6 ADVERSE REACTIONS

The solicited adverse reactions following any dose were irritability (≥55%), crying (≥45%), injection site pain (≥44%), somnolence (≥40%), injection site erythema (≥25%), decreased appetite (≥23%), fever ≥38.0°C (≥19%), injection site swelling (≥18%), and vomiting (≥9%). (6)

To report SUSPECTED ADVERSE REACTIONS, contact Sanofi Pasteur Inc., at 1-800-822-2463 (1-800-VACCINE) or VAERS at 1-800-822-7967 and http://vaers.hhs.gov.

FULL PRESCRIBING INFORMATION

1 INDICATIONS AND USAGE

VAXELIS® is a vaccine indicated for active immunization to prevent diphtheria, tetanus, pertussis, poliomyelitis, hepatitis B, and invasive disease due to Haemophilus influenzae (H. influenzae) type b. VAXELIS is approved for use as a 3-dose series in children 6 weeks through 4 years of age (prior to the 5th birthday).

2 DOSAGE AND ADMINISTRATION

For intramuscular use only.

2.1 Vaccination Schedule

VAXELIS is to be administered as a 3-dose series at 2, 4, and 6 months of age. The first dose may be given as early as 6 weeks of age. Three doses of VAXELIS constitute a primary immunization course against diphtheria, tetanus, H. influenzae type b invasive disease and poliomyelitis.

VAXELIS may be used to complete the hepatitis B immunization series.

A 3-dose series of VAXELIS does not constitute a primary immunization series against pertussis; an additional dose of pertussis-containing vaccine is needed to complete the primary series. [See Pertussis Vaccination Following VAXELIS.]

Pertussis Vaccination following VAXELIS

VAXELIS, Pentacel® [(Diphtheria and Tetanus Toxoids and Acellular Pertussis Adsorbed, Inactivated Poliovirus and Haemophilus b Conjugate (Tetanus Toxoid Conjugate) Vaccine): DTaP-IPV/Hib], Quadracel® [(Diphtheria and Tetanus Toxoids and Acellular Pertussis Adsorbed and Inactivated Poliovirus Vaccine): DTaP-IPV] and DAPTACEL® [(Diphtheria and Tetanus Toxoids and Acellular Pertussis Vaccine Adsorbed): DTaP] contain the same pertussis antigens manufactured by the same process. Children who have received a 3-dose series of VAXELIS should complete the primary and pertussis vaccination series with Pentacel, Quadracel or DAPTACEL according to the respective prescribing information in the approved package inserts. [See ADVERSE REACTIONS (6.1) AND CLINICAL STUDIES (14).]

Administration of VAXELIS following previous doses of other DTaP-containing Vaccines

VAXELIS may be used to complete the first 3 doses of the 5-dose DTaP series in infants and children who have received 1 or 2 doses of Pentacel or DAPTACEL and are also scheduled to receive the other antigens in VAXELIS. Data are not available on the safety and immunogenicity of such mixed sequences.

Data are not available on the safety and effectiveness of using VAXELIS following 1 or 2 doses of a DTaP vaccine from a different manufacturer.

Administration of VAXELIS following previous doses of any Hepatitis B Vaccine

A 3-dose series of VAXELIS may be administered to infants born to HBsAg-negative mothers, and who have received a dose of any hepatitis B vaccine, prior to or at 1 month of age. [See ADVERSE REACTIONS (6.1) AND CLINICAL STUDIES (14).]

VAXELIS may be used to complete the hepatitis B vaccination series following 1 or 2 doses of other hepatitis B vaccines, in infants and children born of HBsAg-negative mothers and who are also scheduled to receive the other antigens in VAXELIS. However, data are not available on the safety and effectiveness of VAXELIS in such infants and children.

Administration of VAXELIS following previous doses of Inactivated Polio Vaccine (IPV)

VAXELIS may be administered to infants and children who have received 1 or 2 doses of IPV and are also scheduled to receive the other antigens in VAXELIS. However, data are not available on the safety and effectiveness of VAXELIS in such infants and children.

Administration of VAXELIS following previous doses of Haemophilus b Conjugate Vaccines

VAXELIS may be administered to infants and children who have received 1 or 2 doses of H. influenzae type b Conjugate Vaccine and are also scheduled to receive the other antigens in VAXELIS. However, data are not available on the safety and effectiveness of VAXELIS in such infants and children.

2.2 Administration

Just before use, shake the vial or syringe until a uniform, white, cloudy suspension results.

Parenteral drug products should be inspected visually for particulate matter and discoloration prior to administration, whenever solution and container permit. If either of these conditions exist, the product should not be administered.

Administer a single 0.5 mL dose of VAXELIS intramuscularly.

In infants younger than 1 year, the anterolateral aspect of the thigh is the preferred site of injection. The vaccine should not be injected into the gluteal area.

VAXELIS should not be combined through reconstitution or mixed with any other vaccine. Discard unused portion.

3 DOSAGE FORMS AND STRENGTHS

VAXELIS is a suspension for injection available in 0.5 mL single-dose vials and prefilled syringes. [See HOW SUPPLIED/STORAGE AND HANDLING (16).]

4 CONTRAINDICATIONS

4.1 Hypersensitivity

Do not administer VAXELIS to anyone with a history of a severe allergic reaction (e.g., anaphylaxis) to a previous dose of VAXELIS, any ingredient of VAXELIS, or any other diphtheria toxoid, tetanus toxoid, pertussis-containing vaccine, inactivated poliovirus vaccine, hepatitis B vaccine, or H. influenzae type b vaccine [See DESCRIPTION (11).]

4.2 Encephalopathy

Do not administer VAXELIS to anyone with a history of encephalopathy (e.g., coma, decreased level of consciousness, prolonged seizures) within 7 days of a previous dose of a pertussis-containing vaccine, that is not attributable to another identifiable cause.

4.3 Progressive Neurologic Disorder

Do not administer VAXELIS to anyone with a history of progressive neurologic disorder, including infantile spasms, uncontrolled epilepsy, or progressive encephalopathy until a treatment regimen has been established and the condition has stabilized.

5 WARNINGS AND PRECAUTIONS

5.1 Management of Acute Allergic Reactions

Epinephrine hydrochloride solution (1:1,000) and other appropriate agents and equipment must be available for immediate use in case an anaphylactic or acute hypersensitivity reaction occurs.

5.2 Adverse Reactions Following Prior Pertussis Vaccination

If any of the following events occur after administration of a pertussis vaccine, the decision to administer VAXELIS should be based on careful consideration of potential benefits and possible risks.

- Temperature of ≥40.5°C (≥105°F) within 48 hours, not attributable to another identifiable cause.
- Collapse or shock-like state (hypotonic-hyporesponsive episode [HHE]) within 48 hours.
- Persistent, inconsolable crying lasting ≥3 hours within 48 hours.
- Seizures with or without fever within 3 days.

5.3 Guillain-Barré Syndrome and Brachial Neuritis

A review by the Institute of Medicine (IOM) found evidence for a causal relation between tetanus toxoid and both brachial neuritis and Guillain-Barré syndrome. If Guillain-Barré syndrome occurred within 6 weeks of receipt of a prior vaccine containing tetanus toxoid, the risk for Guillain-Barré syndrome may be increased following VAXELIS. (1)

5.4 Altered Immunocompetence

If VAXELIS is administered to immunocompromised persons, including persons receiving immunosuppressive therapy, the expected immune response may not be obtained.

5.5 Apnea in Premature Infants

Apnea following intramuscular vaccination has been observed in some infants born prematurely. The decision about when to administer an intramuscular vaccine, including VAXELIS, to an infant born prematurely should be based on consideration of the infant's medical status and the potential benefits and possible risks of vaccination.

5.6 Limitations of Vaccine Effectiveness

Vaccination with VAXELIS may not protect all individuals.

5.7 Interference with Laboratory Tests

Urine antigen detection may not have definitive diagnostic value in suspected H. influenzae type b disease following vaccination with VAXELIS. [See DRUG INTERACTIONS (7.1).]

6 ADVERSE REACTIONS

Rates of adverse reactions varied by number of doses of VAXELIS received. The solicited adverse reactions 0-5 days following any dose were irritability (≥55%), crying (≥45%), injection site pain (≥44%), somnolence (≥40%), injection site erythema (≥25%), decreased appetite (≥23%), fever ≥38.0°C (≥19%), injection site swelling (≥18%), and vomiting (≥9%).

6.1 Clinical Trials Experience

Because clinical trials are conducted under varying conditions, adverse reaction rates observed in the clinical trials of a vaccine cannot be directly compared to rates in the clinical trials of another vaccine and may not reflect the rates observed in practice. The adverse reaction information from clinical trials does, however, provide a basis for identifying the adverse events that appear to be related to vaccine use and for approximating rates of those events.

The safety of VAXELIS was evaluated in 6 clinical studies, in which a total of 5,251 infants 43 to 99 days of age at enrollment received at least 1 dose of VAXELIS. Two of these (study 005 and 006) were controlled clinical studies conducted in the US, in which a total of 3,380 infants 46 to 89 days of age at enrollment received at least 1 dose of VAXELIS. The vaccination schedules of VAXELIS, Control vaccines, and concomitantly administered vaccines used in these studies are provided in Table 1. At 15 months of age, participants in Study 005 received a dose of DAPTACEL and a H. influenzae type b conjugate vaccine, whereas participants in Study 006 received a dose of Pentacel. In a non-US study, 294 children received a dose of VAXELIS at 15 months of age.

Across the 2 studies conducted in the US, among all randomized participants (3,392 in the VAXELIS group and 889 in the Control group), 52.6% were male and 47.4% were female. The race distribution was as follows: 71.7% were White, 11.0% were Black, 4.5% were American Indian or Alaska Native, 3.5% were Asian, and 9.3% were of other racial groups. Most participants (81.8%) were of non-Hispanic or Latino ethnicity. The racial/ethnic distribution of participants who received VAXELIS and Control vaccines was similar.

Table 1: Clinical Safety Studies with VAXELIS in the US: Vaccination Schedules
Study | Vaccine | Concomitantly Administered Vaccines
005 [The first dose of Hepatitis B vaccine was administered prior to study initiation (prior to or at 1 month of age).] | VAXELIS at 2, 4, 6 months and DAPTACEL + PedvaxHIB® at 15 months | RotaTeq® at 2, 4, and 6 months Prevnar 13® at 2, 4, 6, and 15 months
005 [The first dose of Hepatitis B vaccine was administered prior to study initiation (prior to or at 1 month of age).] | Control group vaccines: Pentacel at 2, 4, 6 months and RECOMBIVAX HB® at 2 and 6 months DAPTACEL+ ActHIB® at 15 months | RotaTeq at 2, 4, and 6 months Prevnar 13 at 2, 4, 6, and 15 months
006 | VAXELIS at 2, 4, 6 months and Pentacel at 15 months | RotaTeq at 2, 4, and 6 months Prevnar 13 at 2, 4, 6, and 15 months
006 | Control group vaccines: Pentacel at 2, 4, 6, and 15 months RECOMBIVAX HB at 2 and 6 months | RotaTeq at 2, 4, and 6 months Prevnar 13 at 2, 4, 6, and 15 months
Prevnar 13 (Pneumococcal 13-valent Conjugate Vaccine [Diphtheria CRM197 Protein])
RotaTeq (Rotavirus Vaccine, Live, Oral, Pentavalent)
PedvaxHIB [Haemophilus b Conjugate Vaccine (Meningococcal Protein Conjugate)]
RECOMBIVAX HB (Hepatitis B Vaccine [Recombinant])

Solicited Adverse Reactions

Information on solicited adverse events was recorded daily by parents or guardians on vaccination report cards. The incidence and severity of solicited injection site and systemic adverse reactions (i.e., vaccine-related adverse events) that occurred within 5 days following each dose of VAXELIS or Control vaccines at 2, 4, and 6 months of age in studies 005 and 006 are shown in Table 2.

Table 2: Percentage of Infants with Solicited Adverse Reactions Occurring within 5 days Following VAXELIS or Control Vaccines Administered Concomitantly at Separate Sites with Prevnar 13 and RotaTeq in Studies 005 and 006
 |  | VAXELIS + Prevnar 13 + RotaTeq |  |  | Pentacel + RECOMBIVAX HB + Prevnar 13 + RotaTeq
 |  | Dose 1 (N=3,370) (%) | Dose 2 (N=3,221) (%) | Dose 3 (N=3,134) (%) | Dose 1 (N=880) (%) | Dose 2 (N=849) (%) | Dose 3 (N=825) (%)
Injection Site Adverse Reactions |  | VAXELIS site |  |  | Pentacel or RECOMBIVAX HB site
Injection site erythema | Any | 25.8 | 31.8 | 31.8 | 25.0 | 25.8 | 30.9
Injection site erythema | ≥2.5 cm | 0.9 | 1.0 | 1.3 | 1.1 | 1.1 | 1.2
Injection site erythema | >5.0 cm | 0.0 | 0.1 | 0.2 | 0.3 | 0.2 | 0.1
Injection site pain [Moderate: cries and protests when injection site is touched; Severe: cries when injected limb is moved or the movement of the injected limb is reduced.] | Any | 53.3 | 49.0 | 44.9 | 55.8 | 43.7 | 44.4
Injection site pain [Moderate: cries and protests when injection site is touched; Severe: cries when injected limb is moved or the movement of the injected limb is reduced.] | Moderate or severe | 16.3 | 14.1 | 12.5 | 19.1 | 11.3 | 10.8
Injection site pain [Moderate: cries and protests when injection site is touched; Severe: cries when injected limb is moved or the movement of the injected limb is reduced.] | Severe | 2.8 | 2.5 | 2.0 | 3.2 | 1.9 | 1.3
Injection site swelling | Any | 18.9 | 22.8 | 23.4 | 20.8 | 20.4 | 22.9
Injection site swelling | ≥2.5 cm | 2.5 | 1.6 | 1.7 | 2.7 | 1.3 | 0.8
Injection site swelling | >5.0 cm | 0.2 | 0.2 | 0.2 | 0.3 | 0.1 | 0.0
Systemic Adverse Reactions
Fever | ≥38°C | 19.2 | 29.0 | 29.3 | 14.6 | 18.0 | 17.8
 | ≥38.5°C | 5.3 | 11.5 | 13.2 | 3.4 | 6.5 | 8.1
 | ≥39.5°C | 0.2 | 0.7 | 1.5 | 0.1 | 0.2 | 0.9
Crying | Any | 52.0 | 49.5 | 45.1 | 50.6 | 47.0 | 40.6
 | >1 hour | 18.6 | 19.8 | 16.7 | 20.6 | 16.8 | 14.1
 | >3 hours | 3.6 | 3.8 | 3.4 | 4.4 | 4.0 | 2.9
Decreased Appetite [Moderate: missed 1 or 2 feeds/meals completely; Severe: refuses ≥3 feeds or refuses most feeds.] | Any | 28.9 | 24.2 | 23.2 | 25.8 | 20.5 | 20.1
Decreased Appetite [Moderate: missed 1 or 2 feeds/meals completely; Severe: refuses ≥3 feeds or refuses most feeds.] | Moderate or severe | 7.0 | 5.5 | 4.8 | 6.8 | 3.9 | 5.0
Decreased Appetite [Moderate: missed 1 or 2 feeds/meals completely; Severe: refuses ≥3 feeds or refuses most feeds.] | Severe | 0.5 | 0.5 | 0.5 | 0.6 | 0.2 | 0.0
Irritability [Moderate: requiring increased attention; Severe: inconsolable.] | Any | 61.8 | 58.9 | 55.2 | 61.7 | 56.3 | 51.6
 | Moderate or severe | 24.6 | 23.4 | 20.1 | 25.7 | 19.2 | 16.8
 | Severe | 2.5 | 3.8 | 2.9 | 2.2 | 2.7 | 2.2
Somnolence [Moderate: not interested in surroundings or did not wake up for a meal; Severe: Sleeping most of the time or difficult to wake up.] | Any | 56.3 | 47.8 | 40.8 | 55.2 | 44.1 | 38.8
 | Moderate or severe | 15.0 | 11.5 | 8.5 | 14.5 | 9.4 | 8.2
 | Severe | 1.5 | 1.1 | 1.0 | 1.7 | 0.6 | 1.1
Vomiting [Moderate: 2–5 episodes per 24 hours; Severe: ≥6 episodes per 24 hours or requiring parenteral hydration. A subject with the same adverse reactions at both the Pentacel and RECOMBIVAX HB injection site, was counted once and was classified according to the highest intensity grading. Fever is based upon actual temperatures recorded with no adjustments due to the measurement route. Following Doses 1–3 combined, the proportion of temperature measurements that were taken by rectal, axillary, or other routes were 91.7%, 8.1%, and 0% respectively, for VAXELIS group, and 90.3%, 9.7%, and 0%, respectively, for Pentacel + RECOMBIVAX HB vaccines group.] | Any | 13.1 | 11.5 | 9.5 | 11.3 | 9.7 | 6.9
 | Moderate or severe | 3.5 | 2.6 | 2.1 | 2.8 | 3.1 | 1.0
 | Severe | 0.4 | 0.2 | 0.1 | 0.5 | 0.6 | 0.1
N = Number of vaccinated participants with safety follow-up.

Non-fatal Serious Adverse Events

Across Studies 005 and 006, within 30 days following any infant dose vaccination, 68 participants (2.0%) who received VAXELIS and concomitant vaccines versus 19 participants (2.2%) who received Control and concomitant vaccines experienced a serious adverse event. Of these, a vaccine-related SAE was reported for no participants in the Control vaccines group and for 4 participants (0.1%) in the VAXELIS group:

- 3 of these 4 experienced pyrexia 1 to 2 days following the first study vaccinations; and
- 1 of these 4 experienced an apparent life-threatening event (vomiting followed by pallor and lethargy) on the day of the first study vaccinations, and again 2 days later.

Deaths

In the 2 US studies, death was reported in 6 participants (0.2%) who received VAXELIS and in 1 participant (0.1%) who received Pentacel + RECOMBIVAX HB vaccines; none were assessed as vaccine related. Causes of death among infants who received VAXELIS were sepsis, 2 cases of Sudden Infant Death Syndrome, asphyxia, unknown cause, and hydrocephalus (occurring 2, 10 and 49, 42, 44 days, and 11 months post-vaccination, respectively). Across all 6 clinical studies, there were no deaths assessed as related to VAXELIS.

6.2 Postmarketing Experience

The following adverse events have been reported during post-marketing use of VAXELIS or other vaccines containing the antigens of VAXELIS. These adverse events are included based on a suspected causal connection to VAXELIS or the components of DAPTACEL® (Diphtheria and Tetanus Toxoids and Acellular Pertussis Vaccine Adsorbed), IPOL® (Poliovirus Vaccine Inactivated), COMVAX® [Haemophilus b Conjugate (Meningococcal Protein Conjugate) and Hepatitis B (Recombinant) Vaccine]. (COMVAX is no longer licensed in the US.)

Because these events are reported voluntarily from a population of uncertain size, it is not possible to reliably estimate their frequency or establish a causal relationship to vaccination.

- Immune System Disorders
  Hypersensitivity (such as rash, urticaria, dyspnea, erythema multiforme), anaphylactic reaction (such as urticaria, angioedema, edema, face edema, shock).
- General Disorders and Administration Site Conditions
  Extensive swelling of injected limb (including swelling that involves adjacent joints).
- Nervous System
  Seizure, febrile seizure, hypotonic-hyporesponsive episode (HHE).

7 DRUG INTERACTIONS

7.1 Interference with Laboratory Tests

Sensitive tests (e.g., Latex Agglutination kits) have detected vaccine-derived polyribosylribitol phosphate (PRP) in the urine of vaccinees for at least 30 days following vaccination with PedvaxHIB [Haemophilus b Conjugate Vaccine (Meningococcal Protein Conjugate)]. (2) Therefore, urine antigen detection may not have definite diagnostic value in suspected H. influenzae type b disease following vaccination with VAXELIS. [See WARNINGS AND PRECAUTIONS (5.7).]

8 USE IN SPECIFIC POPULATIONS

8.1 Pregnancy

VAXELIS is not approved for use in individuals 5 years of age and older. No human or animal data are available to assess vaccine-associated risks in pregnancy.

8.2 Lactation

VAXELIS is not approved for use in individuals 5 years of age and older. No human or animal data are available to assess the impact of VAXELIS on milk production, its presence in breast milk, or its effects on the breastfed infant.

8.4 Pediatric Use

The safety of VAXELIS has been established in the age group 6 weeks through 15 months, and the effectiveness of VAXELIS was established in the age group 6 weeks through 6 months on the basis of clinical studies. [See ADVERSE REACTIONS (6.1) AND CLINICAL STUDIES (14).]

The safety and effectiveness of VAXELIS in older children through 4 years of age are supported by evidence in younger children. The safety and effectiveness of VAXELIS in infants less than 6 weeks of age and in children and adolescents 5 through 17 years of age have not been established.

11 DESCRIPTION

VAXELIS (Diphtheria and Tetanus Toxoids and Acellular Pertussis, Inactivated Poliovirus, Haemophilus b Conjugate and Hepatitis B Vaccine) is a sterile suspension for intramuscular injection.

Each 0.5 mL dose is formulated to contain 15 Lf diphtheria toxoid, 5 Lf tetanus toxoid, acellular pertussis antigens [20 mcg detoxified pertussis toxin (PT), 20 mcg filamentous hemagglutinin (FHA), 3 mcg pertactin (PRN), 5 mcg fimbriae types 2 and 3 (FIM)], inactivated polioviruses [29 D-antigen units (DU) Type 1 (Mahoney), 7 DU Type 2 (MEF-1), 26 DU Type 3 (Saukett)], 3 mcg polyribosylribitol phosphate (PRP) of H. influenzae type b covalently bound to 50 mcg of the outer membrane protein complex (OMPC) of Neisseria meningitidis serogroup B, and 10 mcg hepatitis B surface antigen (HBsAg). Each 0.5 mL dose contains 319 mcg aluminum from aluminum salts used as adjuvants.

Other ingredients per 0.5 mL dose include <0.0056% polysorbate 80 and the following residuals from the manufacturing process: ≤14 mcg formaldehyde, ≤50 ng glutaraldehyde, ≤50 ng bovine serum albumin, <5 ng of neomycin, <200 ng streptomycin sulfate, <25 ng polymyxin B sulfate, ≤0.125 μg ammonium thiocyanate and ≤0.1 mcg yeast protein (maximum 1% relative to HBsAg protein).

Corynebacterium diphtheriae is grown in modified Mueller's growth medium. (3) After purification by ammonium sulfate fractionation, the diphtheria toxin is detoxified with formaldehyde and diafiltered.

Clostridium tetani is grown in modified Mueller-Miller casamino acid medium without beef heart infusion. (4) Tetanus toxin is detoxified with formaldehyde and purified by ammonium sulfate fractionation and diafiltration. Diphtheria and tetanus toxoids are individually adsorbed onto aluminum phosphate.

The acellular pertussis vaccine antigens are produced from Bordetella pertussis cultures grown in Stainer-Scholte medium (5) modified by the addition of casamino acids and dimethyl-beta-cyclodextrin. PT, FHA and PRN are isolated separately from the supernatant culture medium. FIM are extracted and copurified from the bacterial cells. The pertussis antigens are purified by sequential filtration, salt-precipitation, ultrafiltration and chromatography. PT is detoxified with glutaraldehyde. FHA is treated with formaldehyde and the residual aldehydes are removed by ultrafiltration. The individual antigens are adsorbed separately onto aluminum phosphate.

The Type 1, Type 2, and Type 3 polioviruses are individually grown in Vero cells. The viral harvests are concentrated and purified, then inactivated with formaldehyde to produce monovalent suspensions of each serotype. Specified quantities of monovalent suspensions of each serotype are mixed to produce the trivalent poliovirus concentrate.

The HBsAg antigen is harvested and purified from fermentation cultures of a recombinant strain of the yeast Saccharomyces cerevisiae containing the gene for the adw subtype of HBsAg. The recombinant Saccharomyces cerevisiae is grown in a fermentation medium which consists of an extract of yeast, soy peptone, dextrose, amino acids, and mineral salts. The HBsAg protein is released from the yeast cells by cell disruption and purified by a series of physical and chemical methods which includes ion and hydrophobic chromatography, and diafiltration. The purified protein is treated in phosphate buffer with formaldehyde and then co-precipitated with alum (potassium aluminum sulfate) to form bulk vaccine adjuvanted with amorphous aluminum hydroxyphosphate sulfate.

The purified PRP of H. influenzae type b (Haemophilus b, Ross strain) is conjugated to an OMPC of the B11 strain of N. meningitidis serogroup B. H. influenzae type b is grown in a fermentation medium which includes an extract of yeast, nicotinamide adenine dinucleotide, hemin chloride, soy peptone, dextrose, and mineral salts. The PRP is purified from the culture broth by purification procedures which include ethanol fractionation, enzyme digestion, phenol extraction and diafiltration. N. meningitidis serogroup B is grown in a fermentation medium which includes an extract of yeast, amino acids and mineral salts. The OMPC is purified by detergent extraction, ultracentrifugation, diafiltration and sterile filtration. PRP is conjugated to OMPC by chemical coupling and the PRP-OMPC is then adsorbed onto an amorphous aluminum hydroxyphosphate sulfate adjuvant.

The adsorbed diphtheria, tetanus, and acellular pertussis antigens are combined with aluminum phosphate (as adjuvant) and water for injection into an intermediate concentrate. The individual HBsAg and PRP-OMPC adjuvanted bulks are added followed by the trivalent poliovirus concentrate, to produce VAXELIS.

Both diphtheria and tetanus toxoids induce at least 2 neutralizing units per mL of serum in the guinea pig potency test. The potency of the PT, FHA, and FIM components of the acellular pertussis antigens are evaluated by the antibody response of immunized mice to detoxified PT, FHA and FIM as measured by enzyme-linked immunosorbent assay (ELISA). The potency of the PRN component of the acellular pertussis antigens is measured relative to a standard by in vitro PRN antigenicity ELISA. The potency of the inactivated polioviruses is evaluated using the in vitro D-antigen ELISA for each serotype, relative to a standard. The potency of the HBsAg component is measured relative to a standard by an in vitro immunoassay. The potency of the PRP-OMPC component is measured by quantitating the polysaccharide concentration using an HPLC method.

VAXELIS does not contain a preservative. The vial stopper, syringe plunger stopper, and syringe tip cap are not made with natural rubber latex.

12 CLINICAL PHARMACOLOGY

12.1 Mechanism of Action

Diphtheria

Diphtheria is an acute toxin-mediated disease caused by toxigenic strains of C. diphtheriae. Protection against disease is due to the development of neutralizing antibodies to diphtheria toxin. A serum diphtheria antitoxin level of 0.01 IU/mL is the lowest level giving some degree of protection. Antitoxin levels of ≥0.1 IU/mL are generally regarded as protective. (6) Levels of 1.0 IU/mL have been associated with long-term protection. (7)

Tetanus

Tetanus is an acute disease caused by an extremely potent neurotoxin produced by C. tetani. Protection against disease is due to the development of neutralizing antibodies to tetanus toxin. A serum tetanus antitoxin level of ≥0.01 IU/mL, measured by neutralization assay is considered the minimum protective level. (6) (8) A tetanus antitoxoid level ≥0.1 IU/mL as measured by the ELISA used in clinical studies of VAXELIS is considered protective.

Pertussis

Pertussis (whooping cough) is a respiratory disease caused by B. pertussis. This Gram-negative coccobacillus produces a variety of biologically active components, though their role in either the pathogenesis of, or immunity to, pertussis has not been clearly defined.

Poliomyelitis

Polioviruses, of which there are 3 serotypes (Types 1, 2, and 3), are enteroviruses. The presence of poliovirus type-specific neutralizing antibodies has been correlated with protection against poliomyelitis. (9)

Hepatitis B

Hepatitis B virus is one of several hepatitis viruses that cause systemic infection, with major pathology in the liver. Antibody concentrations of ≥10 mIU/mL against HBsAg correlate with protection against hepatitis B virus infection.

Haemophilus influenzae type b Invasive Disease

H. influenzae type b can cause invasive disease such as meningitis and sepsis. Anti-PRP antibody has been shown to correlate with protection against invasive disease due to H. influenzae type b.

Based on data from passive antibody studies (10) and an efficacy study with H. influenzae type b polysaccharide vaccine in Finland, (11) a post-vaccination anti-PRP level of ≥0.15 mcg/mL is considered a minimal protective level. Data from an efficacy study with H. influenzae type b polysaccharide vaccine in Finland indicate that an anti-PRP level of ≥1.0 mcg/mL 3 weeks after vaccination predicts protection through a subsequent 1-year period. (11) (12) These levels have been used to evaluate the effectiveness of H. influenzae type b conjugate vaccines, including the PRP-OMPC component of VAXELIS.

13 NONCLINICAL TOXICOLOGY

13.1 Carcinogenesis, Mutagenesis, Impairment of Fertility

VAXELIS has not been evaluated for carcinogenic or mutagenic potential or impairment of fertility.

14 CLINICAL STUDIES

14.1 Effectiveness of VAXELIS

The effectiveness of VAXELIS is based on the immunogenicity of the individual antigens compared to US licensed vaccines. Serological correlates of protection exist for diphtheria, tetanus, hepatitis B, poliomyelitis, and invasive disease due to H. influenzae type b. The effectiveness against pertussis is based upon the pertussis immune responses following 3 doses of VAXELIS compared to 3 doses of Pentacel, as well as the pertussis immune responses following a subsequent dose of DAPTACEL in the same 2 groups of children. VAXELIS, Pentacel and DAPTACEL contain the same pertussis antigens, manufactured by the same processes.

14.2 Immunogenicity

In the US Study 005 (Table 1), infants were randomized to receive 3 doses of VAXELIS at 2, 4, and 6 months of age and DAPTACEL and PedvaxHIB at 15 months of age, or Control group vaccines (3 doses of Pentacel vaccine at 2, 4, and 6 months of age + RECOMBIVAX HB at 2 and 6 months of age and DAPTACEL and ActHIB at 15 months of age). All subjects received concomitant vaccines: RotaTeq at 2, 4 and 6 months and Prevnar 13 at 2, 4, 6, and 15 months of age. [See ADVERSE REACTIONS (6.1).] All infants had received a dose of hepatitis B vaccine prior to study initiation, prior to or at one month of age. Among all randomized participants, 53.0% were male and 47.0% were female. Most (79.2%) participants were White, 14.1% were Black and 5.2% were multi-racial. Most (91.4%) participants were of non-Hispanic or non-Latin ethnicity.

Antibody responses to diphtheria, tetanus, pertussis (PT, FHA, PRN and FIM), poliovirus types 1, 2 and 3, hepatitis B and H. influenzae type b antigens were measured in sera obtained one month following the third dose of VAXELIS or Pentacel + RECOMBIVAX HB vaccines. VAXELIS was non-inferior to Pentacel + RECOMBIVAX HB administered concomitantly at separate sites, as demonstrated by the proportions of participants achieving seroprotective levels of antibodies to diphtheria, tetanus, poliovirus, hepatitis B and PRP antigens, and pertussis vaccine response rates and GMCs (except FHA), following 3 doses of the vaccine. See Table 3.

To complete the 4-dose pertussis primary vaccination series, participants in both groups received DAPTACEL at 15 months of age and were evaluated for immune responses to pertussis antigens one month later. The non-inferiority criteria for vaccine response rates and GMCs for all pertussis antigens were met following the fourth dose.

Table 3: Antibody Responses One Month Following Dose 3 of VAXELIS or Control Vaccines Administered Concomitantly with Prevnar 13 and RotaTeq in Study 005
 | VAXELIS + Prevnar 13 + RotaTeq (N=688 – 810) | Pentacel + RECOMBIVAX HB + Prevnar 13 + RotaTeq (N=353 – 400)
Anti-Diphtheria Toxoid
% ≥0.1 IU/mL | 82.4 [Non-inferiority criterion met (lower bound of 2-sided 95% CI for the difference [VAXELIS group minus Control vaccines group] was >-10%).] | 86.3
Anti-Tetanus Toxoid
% ≥0.1 IU/mL | 99.9 [Non-inferiority criterion met (lower bound of 2-sided 95% CI for the difference [VAXELIS group minus Control vaccines group] was >-5%).] | 99.5
Anti-PT
% vaccine response [Vaccine response = if pre-vaccination antibody concentration was <4 × lower limit of quantitation [LLOQ], then the post-vaccination antibody concentration was ≥4 × LLOQ; if pre-vaccination antibody concentration was ≥4 × LLOQ, then the post-vaccination antibody concentration was ≥pre-vaccination levels (pre-Dose 1).] | 98.1 | 98.5
GMC | 109.6 [Non-inferiority criterion met (lower bound of 2-sided 95% CI for the GMC ratio [VAXELIS group/Control vaccines group] was >0.67).] | 85.4
Anti-FHA
% vaccine response | 87.3 | 92.0
GMC | 46.6 [Non-inferiority criterion not met for anti-FHA GMC (lower bound of 2-sided 95% CI for the GMC ratio [VAXELIS group/Control vaccines group was 0.59 which is below the non-inferiority criterion >0.67).] | 72.3
Anti-PRN
% vaccine response | 79.3 | 82.0
GMC | 55.8 | 66.8
Anti-FIM
% vaccine response | 90.2 | 86.2
GMC | 235.9 | 184.4
Anti-Poliovirus Type 1
% ≥1:8 dilution | 100.0 | 98.2
Anti-Poliovirus Type 2
% ≥1:8 dilution | 100.0 | 99.7
Anti-Poliovirus Type 3
% ≥1:8 dilution | 100.0 | 99.8
Anti-PRP
% ≥0.15 μg/mL | 97.3 | 92.4
% ≥1.0 μg/mL | 85.0 | 75.3
Anti-HBsAg
% ≥10 mIU/mL | 99.4 | 98.6
N = The number of participants with available data.

Study 006 (Table 1) was a lot consistency study conducted in the US, where infants were randomized to receive 3 doses of VAXELIS at 2, 4, and 6 months of age and Pentacel at 15 months of age (N=2,406), or control group vaccines (4 doses of Pentacel at 2, 4, 6, and 15 months of age + RECOMBIVAX HB at 2 and 6 months of age; N=402). All subjects received concomitant vaccines: RotaTeq at 2, 4 and 6 months and Prevnar 13 at 2, 4, 6, and 15 months of age. All infants had received a dose of hepatitis B vaccine prior to study initiation, from birth up to one month of age.

Antibody responses to diphtheria, tetanus, pertussis (PT, FHA, PRN and FIM), poliovirus types 1, 2 and 3, hepatitis B and H. influenzae type b antigens were measured in sera obtained one month following the third dose of VAXELIS or Pentacel + RECOMBIVAX HB. VAXELIS was non-inferior to Pentacel + RECOMBIVAX HB administered concomitantly at separate sites, as demonstrated by the proportions of participants achieving seroprotective levels of antibodies to diphtheria, tetanus, poliovirus, hepatitis B and PRP antigens, and pertussis vaccine response rates and GMCs, except for GMCs for FHA (lower bound of 2-sided 95% CI for GMC ratio [VAXELIS group/Control group vaccines] was 0.62, which was below the non-inferiority criterion >0.67).

To complete the 4-dose pertussis primary vaccination series, participants in both groups received Pentacel at 15 months of age and were evaluated for immune responses to pertussis antigens one month later. The non-inferiority criteria for antibody vaccine response rates and GMCs for all pertussis antigens were met following the fourth dose except for GMCs for PRN (lower bound of 2-sided 95% CI for GMC ratio [VAXELIS group/Control group vaccines] was 0.66, which was below the non-inferiority criterion >0.67).

14.3 Concomitantly Administered Vaccines

In Study 006 conducted in the US (Table 1), the immune responses to Prevnar 13 were measured one month after the third dose. Non-inferiority criteria were met for GMCs to 12 of the 13 serotype antigens in Prevnar 13 for participants who received VAXELIS relative to Control vaccines. For serotype 6B, the non-inferiority criterion was not met (lower bound of 2-sided 95% CI for GMC ratio [VAXELIS group/Control vaccines group] is 0.64, which is below the non-inferiority criterion >0.67).

15 REFERENCES

1 Stratton K, Ford A, Rusch E, Clayton EW, eds. Institute of Medicine (IOM). Adverse Effects of Vaccines: Evidence and Causality. Washington, DC: The National Academies Press. 2011.
2 Goepp JG, Hohenboken M, Almeido-Hill J, Santosham M. Persistent urinary antigen excretion in infants vaccinated with Haemophilus influenzae type b capsular polysaccharide conjugated with outer membrane protein from Neisseria meningitidis. Pediatr Infect Dis J 1992;11(1):2–5.
3 Stainer DW. Production of diphtheria toxin. In: Manclark CR, editor. Proceedings of an informal consultation on the World Health Organization requirements for diphtheria, tetanus, pertussis and combined vaccines. United States Public Health Service, Bethesda, MD. DHHS 91-1174; 1991. p. 7–11.
4 Mueller JH, Miller PA. Variable factors influencing the production of tetanus toxin. J Bacteriol 1954;67(3):271–7.
5 Stainer DW, Scholte MJ. A simple chemically defined medium for the production of phase I Bordetella pertussis. J Gen Microbiol 1971;63:211–20.
6 Department of Health and Human Services, Food and Drug Administration. Biological products; bacterial vaccines and toxoids; implementation of efficacy review; proposed rule. Federal Register 1985;50(240):51002–117.
7 Tiwari TSP, Wharton M. Diphtheria toxoid. In: Plotkin SA, Orenstein WA, and Offit PA, editors. Vaccines. 6th ed. Philadelphia, PA: WB Saunders; 2013:153–66.
8 Roper M, Wassilak SGF, Tiwari TSP, Orenstein WA. Tetanus toxoid. In: Plotkin SA, Orenstein WA, Offit PA, editors. Vaccines. 6th ed. Philadelphia, PA: WB Saunders; 2013. p. 746–72.
9 Sutter RW, et al. Defining surrogate serologic tests with respect to predicting protective vaccine efficacy: Poliovirus vaccination. In: Williams JC, et al. eds. Combined vaccines and simultaneous administration. Current issues and perspectives. New York, NY: The New York Academy of Sciences. 1995:289–99.
10 Robbins, J. B., et al: Quantitative measurement of 'natural' and immunization-induced Haemophilus influenzae type b capsular polysaccharide antibodies. Pediatr Res 1973;7(3):103–10.
11 Kayhty H, et al. The protective level of serum antibodies to the capsular polysaccharide of Haemophilus influenzae type b. J Infect Dis 1983;147:1100.
12 Anderson P. The protective level of serum antibodies to the capsular polysaccharide of Haemophilus influenzae type b. J Infect Dis 1984;149:1034.

16 HOW SUPPLIED/STORAGE AND HANDLING

16.1 How Supplied

Single-dose vial (NDC 63361-243-58) in packages of 10 vials (NDC 63361-243-10).

Single-dose, prefilled syringe with Luer lock connection and a tip cap, without needle, 0.5 mL (NDC 63361-243-88). Supplied as package of 10 (NDC 63361-243-15).

The vial stopper, syringe plunger stopper, and syringe tip cap are not made with natural rubber latex.

16.2 Storage and Handling

VAXELIS should be stored at 2°C to 8°C (36°F to 46°F). Do not freeze. Product which has been exposed to freezing should not be used. Protect from light. Do not use after expiration date shown on the label. Discard unused portion.

17 PATIENT COUNSELING INFORMATION

Advise the patient to read the FDA-approved patient labeling (Patient Information).

Inform the parent or guardian of the following:

- The potential benefits and risks of immunization with VAXELIS.
- The common adverse reactions that have occurred following administration of VAXELIS or other vaccines containing similar ingredients.
- Other adverse reactions can occur. Call healthcare provider with any adverse reactions of concern.

Provide the Vaccine Information Statements (VIS), which are required by the National Childhood Vaccine Injury Act of 1986.

Manufactured by:
Sanofi Pasteur Limited
Toronto, Ontario, Canada
for:
MSP Vaccine Company
Swiftwater, PA 18370, USA

Distributed by:
Merck Sharp & Dohme LLC
Rahway, NJ 07065, USA
and Sanofi Pasteur Inc.
Swiftwater, PA 18370, USA

VAXELIS is a trademark of MSP Vaccine Company. The trademarks depicted herein are owned by their respective companies.

R11-1125 USA

Patient Information

VAXELIS® (pronounced "vak-sel-lis")
(Diphtheria and Tetanus Toxoids and Acellular Pertussis, Inactivated Poliovirus, Haemophilus b Conjugate and Hepatitis B Vaccine)

Before your child gets VAXELIS, read this document and be sure you understand all of the information. Keep this document, you may need to read it again. If you have questions or side effects, ask your child's healthcare provider. This information does not take the place of talking about VAXELIS with your child's healthcare provider.

What is VAXELIS?

VAXELIS is a vaccine given to protect your child from getting diphtheria, tetanus (lockjaw), pertussis (whooping cough), polio, Hib (Haemophilus influenzae type b), and hepatitis B.

Your child cannot get any of these diseases from VAXELIS.

VAXELIS may not completely protect your child from these diseases.

Who should not get VAXELIS?

Your child should not get VAXELIS, if your child:

- is allergic to any of the ingredients.
- had an allergic reaction to any prior shot for diphtheria, tetanus, pertussis, polio, Hib, or hepatitis B.
- had a serious reaction affecting their brain and nervous system after a whooping cough shot.
- has a brain and nerve illness that is getting worse.

Before your child gets VAXELIS, tell your healthcare provider if your child:

- had problems with any shots for these diseases.
- is taking steroids, getting treatment for cancer, or has another problem that weakens the immune system.

How is VAXELIS given?

- VAXELIS is given to children from 6 weeks through 4 years of age (up to 5th birthday).
- Your child will need 3 shots:
  - one shot at 2 months old, and
  - one shot at 4 months old, and
  - one shot at 6 months old

- If your child misses a shot of VAXELIS, your healthcare provider may suggest a catch-up schedule.
- Your child may get VAXELIS at the same time they get other vaccines.

What are the most common side effects of VAXELIS?

- pain, redness, or swelling where the shot was given
- fever (100.4°F or higher)
- crying more than usual
- eating less than usual
- fussy more than usual
- sleepy more than usual
- throwing up

There may be other side effects that are not listed. If your child has any side effects that worry you or seem to get worse, tell your child's healthcare provider right away.

You may report any side effects directly to the Vaccine Adverse Event Reporting System (VAERS) at 1-800-822-7967 or http://vaers.hhs.gov, or contact Sanofi Pasteur Inc., at 1-800-822-2463 (1-800-VACCINE).

To learn more about VAXELIS, ask your healthcare provider. You can also find the Full Prescribing Information written for doctors at www.fda.gov/media/119465/download.

What is in VAXELIS?

- Active ingredients: inactivated bacteria of diphtheria, tetanus, pertussis, Hib, and inactivated hepatitis B and polio viruses. The bacteria and viruses in VAXELIS are not alive and do not cause disease.
- Other ingredients: aluminum salts, polysorbate 80, glutaraldehyde, formaldehyde, bovine serum albumin, neomycin, streptomycin, polymyxin B, ammonium thiocyanate, yeast protein, and water.
- VAXELIS does not have any preservatives in it.
- VAXELIS vial stopper, syringe plunger stopper, and syringe tip cap do not contain natural rubber latex.

Manufactured by: Sanofi Pasteur Limited
Toronto, Ontario, Canada for: MSP Vaccine Company Swiftwater, PA 18370, USA.
Distributed by: Merck Sharp & Dohme LLC,
Rahway, NJ 07065, USA,
and by Sanofi Pasteur Inc.
Swiftwater, PA 18370, USA.
VAXELIS is a trademark of MSP Vaccine Company. The trademarks depicted herein are owned by their respective companies.
Initial Approval: 23 October 2020
R3-0725

PRINCIPAL DISPLAY PANEL - 0.5 mL Vial Label

DTaP-IPV-Hib-HepB
NDC 63361-243-58

6 wks - 4 yrs
Single-dose
(0.5 mL) IM

Diphtheria and Tetanus
Toxoids and Acellular Pertussis,
Inactivated Poliovirus,
Haemophilus b Conjugate
and Hepatitis B Vaccine
Vaxelis®

Rx only

Mfd by: Sanofi Pasteur Limited

PRINCIPAL DISPLAY PANEL - 0.5 mL Vial Package

NDC 63361-243-10

DTaP-IPV-Hib-HepB
10 single-dose vials

Diphtheria and Tetanus Toxoids
and Acellular Pertussis,
Inactivated Poliovirus,
Haemophilus b Conjugate
and Hepatitis B Vaccine

Vaxelis®

For children 6 weeks through 4 years of age
Rx only

MERCK
sanofi

PRINCIPAL DISPLAY PANEL - 0.5 mL Syringe Label

DTaP-IPV-Hib-HepB
NDC 63361-243-88

6 wks - 4 yrs
Single-dose
(0.5 mL) IM

Diphtheria and Tetanus
Toxoids and Acellular Pertussis,
Inactivated Poliovirus,
Haemophilus b Conjugate
and Hepatitis B Vaccine
Vaxelis®

Rx only

Mfd by: Sanofi Pasteur Limited
358

PRINCIPAL DISPLAY PANEL - 0.5 mL Syringe Package

NDC 63361-243-15

DTaP-IPV-Hib-HepB
10 single-dose prefilled syringes

Diphtheria and Tetanus Toxoids
and Acellular Pertussis,
Inactivated Poliovirus,
Haemophilus b Conjugate
and Hepatitis B Vaccine

Vaxelis®

Rx only

For children 6 weeks through 4 years of age

MERCK

sanofi